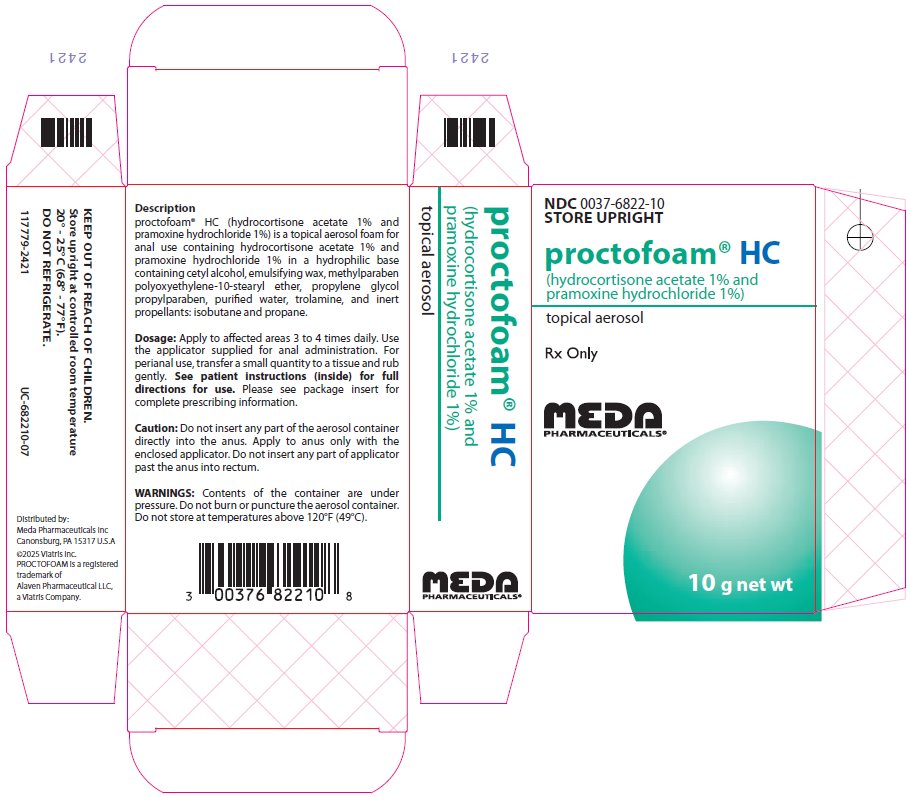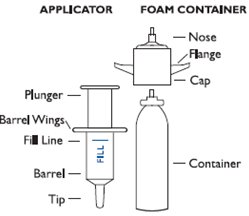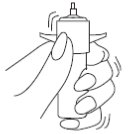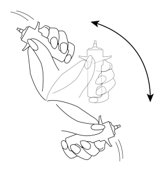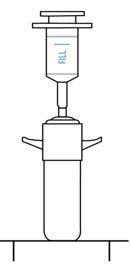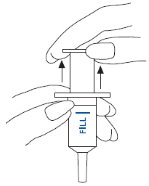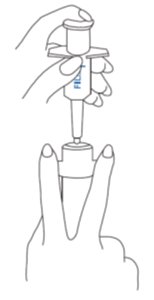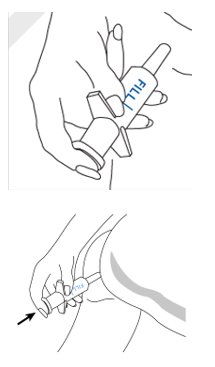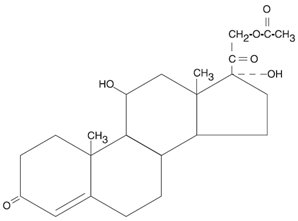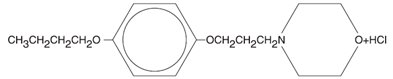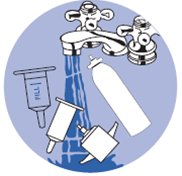 DRUG LABEL: PROCTOFOAM
NDC: 0037-6822 | Form: AEROSOL, FOAM
Manufacturer: Viatris Specialty LLC
Category: prescription | Type: HUMAN PRESCRIPTION DRUG LABEL
Date: 20250415

ACTIVE INGREDIENTS: PRAMOXINE HYDROCHLORIDE 100 mg/10 g; HYDROCORTISONE ACETATE 100 mg/10 g
INACTIVE INGREDIENTS: PROPYLENE GLYCOL; CETYL ALCOHOL; PEG-100 STEARATE; PROPYLPARABEN; METHYLPARABEN; TROLAMINE; WATER; ISOBUTANE; PROPANE; ETHYLENE DISTEARAMIDE

DESCRIPTION

Proctofoam® HC (hydrocortisone acetate 1% and pramoxine hydrochloride 1%) is a topical aerosol foam for anal use containing hydrocortisone acetate 1% and pramoxine hydrochloride 1% in a hydrophilic base containing cetyl alcohol, emulsifying wax, methylparaben, poly-oxyethylene-10-stearyl ether, propylene glycol, propylparaben, purified water, trolamine and inert propellants: isobutane and propane.

Proctofoam® HC contains a synthetic corticosteroid used as an anti-inflammatory/antipruritic agent and a local anesthetic.

Hydrocortisone acetate

Molecular weight: 404.50. Solubility of hydrocortisone acetate in water: 1 mg/100 mL.

Chemical name: pregn-4-ene-3,20-dione, 21-(acetyloxy)-11,17-dihydroxy-,(11β)-.

Pramoxine hydrochloride

Molecular weight: 329.86. Pramoxine hydrochloride is freely soluble in water. Chemical name: morpholine, 4-[3-(4-butoxyphenoxy) propyl]-, hydrochloride.

CLINICAL PHARMACOLOGY

Topical corticosteroids share anti-inflammatory, antipruritic and vasoconstrictive actions.

The mechanism of anti-inflammatory activity of the topical corticosteroids is unclear. Various laboratory methods, including vasoconstrictor assays, are used to compare and predict potencies and/or clinical efficacies of the topical corticosteroids. There is some evidence to suggest that a recognizable correlation exists between vasoconstrictor potency and therapeutic efficacy in man.

Pramoxine hydrochloride is a surface or local anesthetic which is not chemically related to the "caine" types of local anesthetics. Its unique chemical structure is likely to minimize the danger of cross-sensitivity reactions in patients allergic to other local anesthetics.

Pharmacokinetics

The extent of percutaneous absorption of topical corticosteroids is determined by many factors including the vehicle, the integrity of the epidermal barrier, and the use of occlusive dressings.

Topical corticosteroids can be absorbed through normal intact skin. Inflammation and/or other disease processes in the skin increase the percutaneous absorption of topical corticosteroids. Occlusive dressings substantially increase the percutaneous absorption of topical corticosteroids. Thus, occlusive dressings may be a valuable therapeutic adjunct for treatment of resistant dermatoses. (See DOSAGE AND ADMINISTRATION.)

Once absorbed through the skin, topical corticosteroids are handled through pharmacokinetic pathways similar to systemically administered corticosteroids. Corticosteroids are bound to plasma proteins in varying degrees. Corticosteroids are metabolized primarily in the liver and are then excreted by the kidneys. Some of the topical corticosteroids and their metabolites are also excreted into the bile.

INDICATIONS AND USAGE

Proctofoam® HC is indicated for the relief of the inflammatory and pruritic manifestations of corticosteroid-responsive dermatoses of the anal region.

CONTRAINDICATIONS

Topical corticosteroid products are contraindicated in those patients with a history of hypersensitivity to any of the components of the preparation.

WARNINGS

Do not insert any part of the aerosol container directly into the anus. Avoid contact with the eyes. Contents of the container are under pressure. Do not burn or puncture the aerosol container. Do not store at temperatures above 120°F (49°C). If there is no evidence of clinical improvement within two or three weeks after starting Proctofoam® HC therapy, or if the patient's condition worsens, discontinue the drug. Keep this and all medicines out of the reach of children.

PRECAUTIONS

General

Systemic absorption of topical corticosteroids has produced reversible hypothalamic-pituitary-adrenal (HPA) axis suppression, manifestations of Cushing's syndrome, hyperglycemia, and glucosuria in some patients.

Conditions which augment systemic absorption include the application of the more potent steroids, use over large surface areas, prolonged use, and the addition of occlusive dressings. Therefore, patients receiving a large dose of a potent topical steroid applied to a large surface area or under an occlusive dressing should be evaluated periodically for evidence of HPA axis suppression by using the urinary free cortisol and ACTH stimulation tests. If HPA axis suppression is noted, an attempt should be made to withdraw the drug, to reduce the frequency of application or to substitute a less potent steroid.

Recovery of HPA axis function is generally prompt and complete upon discontinuation of the drug. Infrequently, signs and symptoms of steroid withdrawal may occur, requiring supplemental systemic corticosteroids. Pediatric patients may absorb proportionally larger amounts of topical corticosteroids and thus be more susceptible to systemic toxicity. (see PRECAUTIONS: Pediatric Use.)

If irritation develops, topical corticosteroids should be discontinued and appropriate therapy instituted.

In the presence of dermatological infections, the use of an appropriate antifungal or antibacterial agent should be instituted. If a favorable response does not occur promptly, the corticosteroid should be discontinued until the infection has been adequately controlled.

Information for the Patient

Patients using topical corticosteroids should receive the following information and instructions:

1. This medication is to be used as directed by the physician. It is for anal or perianal use only. Avoid contact with eyes.
2. Be advised not to use this medication for any disorder other than for which it has been prescribed.
3. Report any signs of adverse reactions.

Laboratory Tests

The following tests may be helpful in evaluating the HPA axis suppression:

Urinary free cortisol test

ACTH stimulation test

Carcinogenesis, Mutagenesis, Impairment of Fertility

Long-term animal studies have not been performed to evaluate the carcinogenic potential or the effect on fertility of topical corticosteroids.

Studies to determine mutagenicity with prednisolone and hydrocortisone have revealed negative results.

Pregnancy

Teratogenic Effects

Corticosteroids are generally teratogenic in laboratory animals when administered systemically at relatively low dosage levels. The more potent corticosteroids have been shown to be teratogenic after dermal application in laboratory animals. There are no adequate, well-controlled studies of teratogenic effects from topically applied corticosteroids in pregnant women. Therefore, topical corticosteroids should be used during pregnancy only if the potential benefit justifies the potential risk to the fetus. Drugs of this class should not be used extensively on pregnant patients, in large amounts, or for prolonged periods of time.

Nursing Mothers

It is not known whether topical administration of corticosteroids could result in sufficient systemic absorption to produce detectable quantities in breast milk. Systemically administered corticosteroids are secreted into breast milk in quantities not likely to have a deleterious effect on the infant. Nevertheless, caution should be exercised when topical corticosteroids are administered to a nursing woman.

Pediatric Use

Pediatric patients may demonstrate greater susceptibility to topical corticosteroid-induced HPA axis suppression and Cushing's syndrome than mature patients because of a larger skin surface area to body weight ratio.

Hypothalamic-pituitary-adrenal (HPA) axis suppression, Cushing's syndrome, and intracranial hypertension have been reported in pediatric patients receiving topical corticosteroids. Manifestations of adrenal suppression in pediatric patients include linear growth retardation, delayed weight gain, low plasma cortisol levels, and absence of response to ACTH stimulation. Manifestations of intracranial hypertension include bulging fontanelles, headaches, and bilateral papilledema.

Administration of topical corticosteroids to pediatric patients should be limited to the least amount compatible with an effective therapeutic regimen. Chronic corticosteroid therapy may interfere with the growth and development of pediatric patients.

Geriatric Use

Reported clinical experience has not identified differences in responses between the elderly and younger patients. In general, dose selection for an elderly patient should be cautious using the least amount compatible with an effective therapeutic regimen and reflecting the greater frequency of decreased hepatic, renal or cardiac function, and of concomitant disease or other drug therapy.

ADVERSE REACTIONS

The following local adverse reactions are reported infrequently with topical corticosteroids, but may occur more frequently with the use of occlusive dressings. These reactions are listed in approximate decreasing order of occurrence: burning, itching, irritation, dryness, folliculitis, hypertrichosis, acneiform eruptions, hypopigmentation, perioral dermatitis, allergic contact dermatitis, maceration of the skin, secondary infection, skin atrophy, striae and miliaria.

To report SUSPECTED ADVERSE REACTIONS, contact Meda Pharmaceuticals Inc. at 1-866-210-5948 or FDA at 1-800-FDA-1088 or www.fda.gov/medwatch.

OVERDOSAGE

Topically applied corticosteroids can be absorbed in sufficient amounts to produce systemic effects. (See PRECAUTIONS.)

DOSAGE AND ADMINISTRATION

Apply to affected area 3 to 4 times daily. Use the applicator supplied for anal administration. For perianal use, transfer a small quantity to a tissue and rub in gently.

Directions for Use.

1. Attach Cap: Place cap on top of container.
2. Shake Container: Shake foam container vigorously for 5-10 seconds before each use. Do not remove container cap during use of the product.
3. Attach Applicator: Hold container upright on a level surface and gently place the tip of the applicator onto the nose of the container cap. CONTAINER MUST BE HELD UPRIGHT TO OBTAIN PROPER FLOW OF MEDICATION.
4. Pull Plunger: Pull plunger past the fill line on the applicator barrel.
5. Prime Container: Hold the container and applicator at eye level. Place the index and middle fingers on the container cap flanges and the thumb beneath the container. Support the applicator with your other hand. Prime the container by pressing down firmly on flanges and then release. With initial priming, a burst of air may come out of the container. It usually requires 1-2 pumps for foam to appear.
6. Fill Applicator: To fill applicator barrel, press down firmly on cap flanges, hold for 1-2 seconds, and release. Wait 5-10 seconds to allow foam to expand in applicator barrel. Repeat until foam reaches fill line. It usually requires 3-4 pumps for foam to reach fill line. Remove applicator from container cap. Note: If foam goes beyond fill line, it will continue to expand and flow backwards resulting in foam build-up under cap.
7. Foam Application: Hold applicator firmly by barrel, making sure thumb and middle finger are positioned securely underneath and resting against barrel wings. Place index finger over the plunger. Gently insert tip into anus. Once in place, push plunger to expel foam, then withdraw applicator. CAUTION: Do not insert any part of the aerosol container directly into the anus. Apply to anus only with enclosed applicator. Do not insert any part of the applicator past the anus into rectum.
8. Clean Applicator: After each use, applicator parts should be pulled apart for thorough cleaning with warm water. Since some foam will appear under the cap, the cap and underlying tip should be pulled apart and rinsed to help prevent build-up of foam and possible blockage.

HOW SUPPLIED

Proctofoam® HC is supplied in an aerosol container with a special anal applicator. When used correctly, the aerosol container will deliver a minimum of 14 applications.

NDC 0037-6822-10 10 g

Store upright at controlled room temperature 20°-25°C (68°-77°F). DO NOT REFRIGERATE.

Distributed by:
Meda Pharmaceuticals Inc.
Canonsburg, PA 15317 U.S.A.

© 2025 Viatris Inc.

PROCTOFOAM is a registered trademark of Alaven Pharmaceutical LLC, a Viatris Company.

IN-682210-05

141371-0421

Patient Instructions

PLEASE READ CAREFULLY BEFORE USING

PATIENT INSTRUCTIONS FOR

proctofoam® HC

(hydrocortisone acetate 1% and
pramoxine hydrochloride 1%)

TOPICAL AEROSOL

Keep this insert. It contains

important information about

the use of proctofoam® HC.

1 Attach Cap: Place cap on top of container.

2 Shake Container: Shake foam container vigorously for 5-10 seconds before each use. Do not remove container cap during use of the product.

3 Attach Applicator: Hold container upright on a level surface and gently place the tip of the applicator onto the nose of the container cap. CONTAINER MUST BE HELD UPRIGHT TO OBTAIN PROPER FLOW OF MEDICATION.

4 Pull Plunger: Pull plunger past the fill line on the applicator barrel.

5 Prime Container: Hold the container and applicator at eye level. Place the index and middle fingers on the container cap flanges and the thumb beneath the container. Support the applicator with your other hand. Prime the container by pressing down firmly on flanges and then release. With initial priming, a burst of air may come out of the container. It usually requires 1-2 pumps for foam to appear.

6 Fill Applicator: To fill applicator barrel, press down firmly on cap flanges, hold for 1-2 seconds, and release. Wait 5-10 seconds to allow foam to expand in applicator barrel. Repeat until foam reaches fill line. It usually requires 3-4 pumps for foam to reach fill line. Remove applicator from container cap. Note: If foam goes beyond fill line, it will continue to expand and flow backwards resulting in foam build-up under cap.

7 Foam Application: Hold applicator firmly by barrel, making sure thumb and middle finger are positioned securely underneath and resting against barrel wings. Place index finger over the plunger. Gently insert tip into anus. Once in place, push plunger to expel foam, then withdraw applicator. CAUTION: Do not insert any part of the aerosol container directly into the anus. Apply to anus only with enclosed applicator. Do not insert any part of the applicator past the anus into rectum.

8 Clean Applicator: After each use, applicator parts should be pulled apart for thorough cleaning with warm water. Since some foam will appear under the cap, the cap and underlying tip should be pulled apart and rinsed to help prevent build-up of foam and possible blockage.

IS-682210-05

141370-0423

Distributed by:
Meda Pharmaceuticals Inc.

Canonsburg, PA 15317 U.S.A.

PROCTOFOAM is a registered trademark of Alaven Pharmaceutical LLC, a Viatris Company.

To report SUSPECTED ADVERSE REACTIONS, contact Meda Pharmaceuticals Inc. at 1-866-210-5948 or FDA at 1-800-FDA-1088 or www.fda.gov/medwatch.

PRINCIPAL DISPLAY PANEL - 10 g

NDC 0037-6822-10
STORE UPRIGHT

proctofoam® HC

(hydrocortisone acetate 1% and
pramoxine hydrochloride 1%)
topical aerosol

Rx Only

10 g net wt

Description
proctofoam® HC (hydrocortisone acetate 1% and
pramoxine hydrochloride 1%) is a topical aerosol foam for
anal use containing hydrocortisone acetate 1% and
pramoxine hydrochloride 1% in a hydrophilic base
containing cetyl alcohol, emulsifying wax, methylparaben
polyoxyethylene-10-stearyl ether, propylene glycol
propylparaben, purified water, trolamine, and inert
propellants: isobutane and propane.

Dosage: Apply to affected areas 3 to 4 times daily. Use
the applicator supplied for anal administration. For
perianal use, transfer a small quantity to a tissue and rub
gently. See patient instructions (inside) for full
directions for use. Please see package insert for
complete prescribing information.

Caution: Do not insert any part of the aerosol container
directly into the anus. Apply to anus only with the
enclosed applicator. Do not insert any part of applicator
past the anus into rectum.

WARNINGS: Contents of the container are under
pressure. Do not burn or puncture the aerosol container.
Do not store at temperatures above 120°F (49°C).

KEEP OUT OF REACH OF CHILDREN.

Store upright at controlled room temperature
20° - 25°C (68° - 77°F).

DO NOT REFRIGERATE.

117779-2421 UC-682210-07

Distributed by:
Meda Pharmaceuticals Inc
Canonsburg, PA 15317 U.S.A

©2025 Viatris Inc.
PROCTOFOAM is a registered
trademark of
Alaven Pharmaceutical LLC,
a Viatris company.